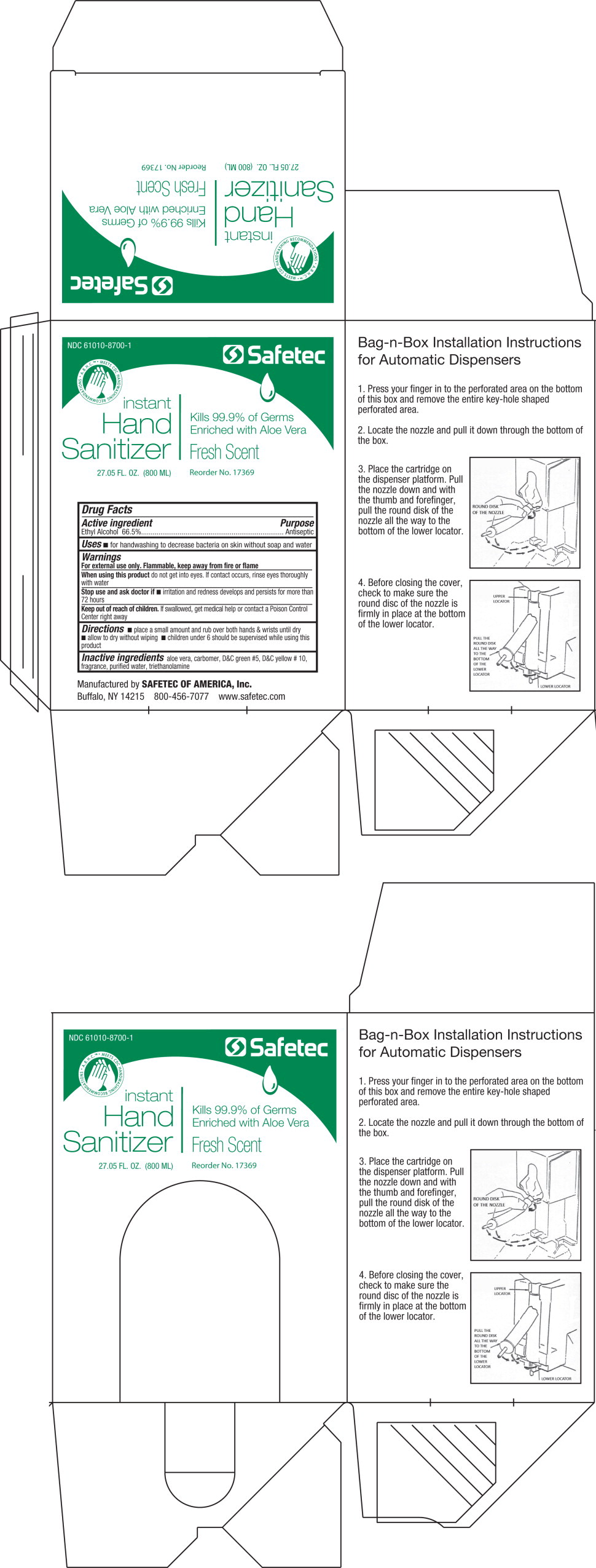 DRUG LABEL: Instant Hand Sanitizer
NDC: 61010-8700 | Form: GEL
Manufacturer: Safetec of America, Inc.
Category: otc | Type: HUMAN OTC DRUG LABEL
Date: 20240204

ACTIVE INGREDIENTS: ALCOHOL 665 mg/1 L
INACTIVE INGREDIENTS: ALOE VERA LEAF; CARBOMER INTERPOLYMER TYPE A (ALLYL SUCROSE CROSSLINKED); WATER; TROLAMINE

61010-8700-1, Hand Sanitizer

Drug Facts

Active Ingredient

Ethyl Alcohol 66.5%

Purpose

Antiseptic

Uses

- for handwashing to decrease bacteria on skin whenever soap and water handwashing is not readily available

Warnings

For external use only. Flammable, keep away from fire or flame

WHEN USING

When using this productdo not get into eyes. If contact occurs, rinse eyes thoroughly with water

Stop use and ask doctor if

- irritation and redness develop and persists for more than 72 hours

Keep out of reach of children.If swallowed, get medical help or contact a Poison Control Center right away

Directions

- place a small amount and rub over both hands and wrists until dry
- allow to dry without wiping
- children under 6 should be supervised while using this product

Inactive ingredients

aloe vera, carbomer, D&C green #5, D&C yellow #10, fragrance, purified water, triethanolamine

Manufactured by SAFETEC OF AMERICA, Inc.
Buffalo, NY 14215 800-456-7077 www.safetec.com

PRINCIPAL DISPLAY PANEL – 27.05 fl. oz. Container Label

NDC 61010-8700-1

Safetec

instant

Hand

Sanitizer Fresh Scent

Kills 99.9% of Germs

Enriched with

Aloe Vera

27.05 fl.oz. (800 ML) Reorder No. 17369